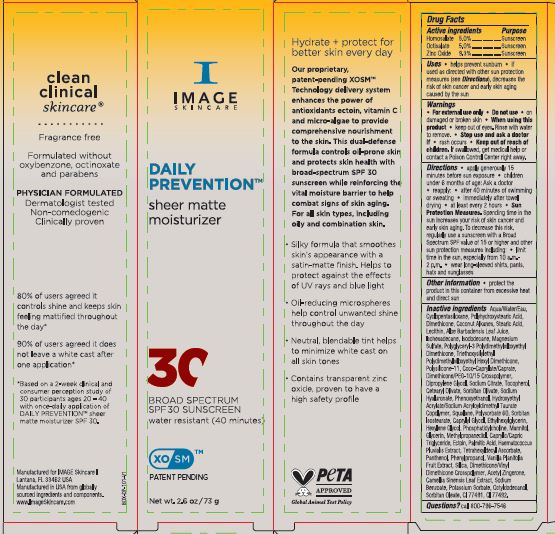 DRUG LABEL: Daily Prevention Sheer Matte Moisturizer SPF30
NDC: 62742-4253 | Form: CREAM
Manufacturer: Allure Labs
Category: otc | Type: HUMAN OTC DRUG LABEL
Date: 20240315

ACTIVE INGREDIENTS: OCTISALATE 5 g/100 g; HOMOSALATE 5 g/100 g; ZINC OXIDE 9.3 g/100 g
INACTIVE INGREDIENTS: GLYCERIN; POLYGLYCERYL-3 POLYDIMETHYLSILOXYETHYL DIMETHICONE (4000 MPA.S); MANNITOL; TETRAHEXYLDECYL ASCORBATE; OCTYLDODECANOL; SORBITAN MONOOLEATE; SODIUM BENZOATE; POTASSIUM SORBATE; DIMETHICONE/VINYL DIMETHICONE CROSSPOLYMER (SOFT PARTICLE); WATER; TRIETHOXYSILYLETHYL POLYDIMETHYLSILOXYETHYL HEXYL DIMETHICONE; HYALURONATE SODIUM; CAPRYLYL GLYCOL; HEXYLENE GLYCOL; SORBITAN ISOSTEARATE; METHYLPROPANEDIOL; ECTOINE; PALMITIC ACID; PANTHENOL; GREEN TEA LEAF; DIPROPYLENE GLYCOL; ISODODECANE; SODIUM CITRATE; TOCOPHEROL; CETEARYL OLIVATE; SORBITAN OLIVATE; FERRIC OXIDE YELLOW; PHOSPHATIDYLCHOLINE TRANSLOCATOR ABCB4; HAEMATOCOCCUS PLUVIALIS; VANILLA; FERRIC OXIDE RED; SQUALANE; ACETYL ZINGERONE; LECITHIN, SOYBEAN; ALOE VERA LEAF; ISOHEXADECANE; HYDROXYETHYL ACRYLATE/SODIUM ACRYLOYLDIMETHYL TAURATE COPOLYMER (45000 MPA.S AT 1%); POLYSORBATE 60; ETHYLHEXYLGLYCERIN; DIMETHICONE; SILICON DIOXIDE; MAGNESIUM SULFATE, UNSPECIFIED; CYCLOMETHICONE 5; COCONUT ALKANES; PHENOXYETHANOL; MEDIUM-CHAIN TRIGLYCERIDES; PHENYLPROPANOL; COCO-CAPRYLATE/CAPRATE; POLYHYDROXYSTEARIC ACID (2300 MW); STEARIC ACID; DIMETHICONE/PEG-10/15 CROSSPOLYMER

Drug Facts

Active ingredients

Homosalate 5.0%

Octisalate 5.0%

Zinc Oxide 9.3%

Purpose: Sunscreen

INDICATIONS AND USAGE

Uses • helps prevent sunburn • if used as directed with other sun protection measures (see Directions), decreases the risk of skin cancer and early skin aging caused by the sun.

Warnings • For external use only

Do not use • on damaged or broken skin

When using this product • keep out of eyes. Rinse with water to remove.

Stop use and ask a doctor if • rash occurs

Keep out of reach of children. If swallowed, get medical help or contact a Poison Control Center right away.

DOSAGE AND ADMINISTRATION

Directions • apply generously 15 minutes before sun exposure • children under 6 months of age: Ask a doctor • reapply: • after 40 minutes of swimming or sweating • immediately after towel drying • at least every 2 hours • Sun Protection Measures. Spending time in the sun increases your risk of skin cancer and early skin aging. To decrease this risk, regularly use a sunscreen with a Broad-Spectrum SPF value of 15 or higher and other sun protection measures including: • limit time in the sun, especially from 10 a.m.-2 p.m. • wear long-sleeved shirts, pants, hats and sunglasses

Other information • protect the product in this container from excessive heat and direct sun

INACTIVE INGREDIENT

Inactive ingredients: Aqua/water/Eau, Cyclopentasiloxane, Polyhydroxystearic Acid, Dimethicone, Coconut Alkanes, Stearic Acid, Lecithin, Aloe Barbadensis Leaf Juice, Isohexadecane, lsododecane, Magnesium Sulfate, Polyglyceryl-3 Polydimethylsiloxyethyl Dimethicone, Triethoxysilylethyl Polydimethylsiloxyethyl Hexyl Dimethicone, Polysillcone-11, Coco-Caprylate/Caprate, Dimethicone/PEG-10/15 Crosspolymer, Dipropylene Glycol, Sodium Citrate, Tocopherol, Cetearyl Olivate, Sorbitan Olivate, Sodium Hyaluronate, Phenoxyethanol, Hydroxyethyl Acrylate/Sodium Acryloyldimethyl Taurate Copolymer, Squalane, Polysorbate 60, Sorbitan Isostearate, Caprylyl Glycol, Ethylhexylycerin, Hexylene Glycol, Phosphatidylcholine, Mannitol, Glycerin, Methylpropanediol, Caprylic/Capric Triglyceride, Ectoine, Palmitic Acid, Haematococcus Pluvialis Extract, Tetrahexyldecyl Ascorbate, Panthenol, Phenylpropanol, Vanilla Planifolia Fruit Extract, Silica, Dimethicone/Vinyl Dimethicone Crosspolymer, Acetyl Zingerone, Camellia Sinensis Leaf Extract, Sodium Benzoate, Potassium Sorbate, Octyldodecanol, Sorbitan Oleate, CI 77491, CI 77492